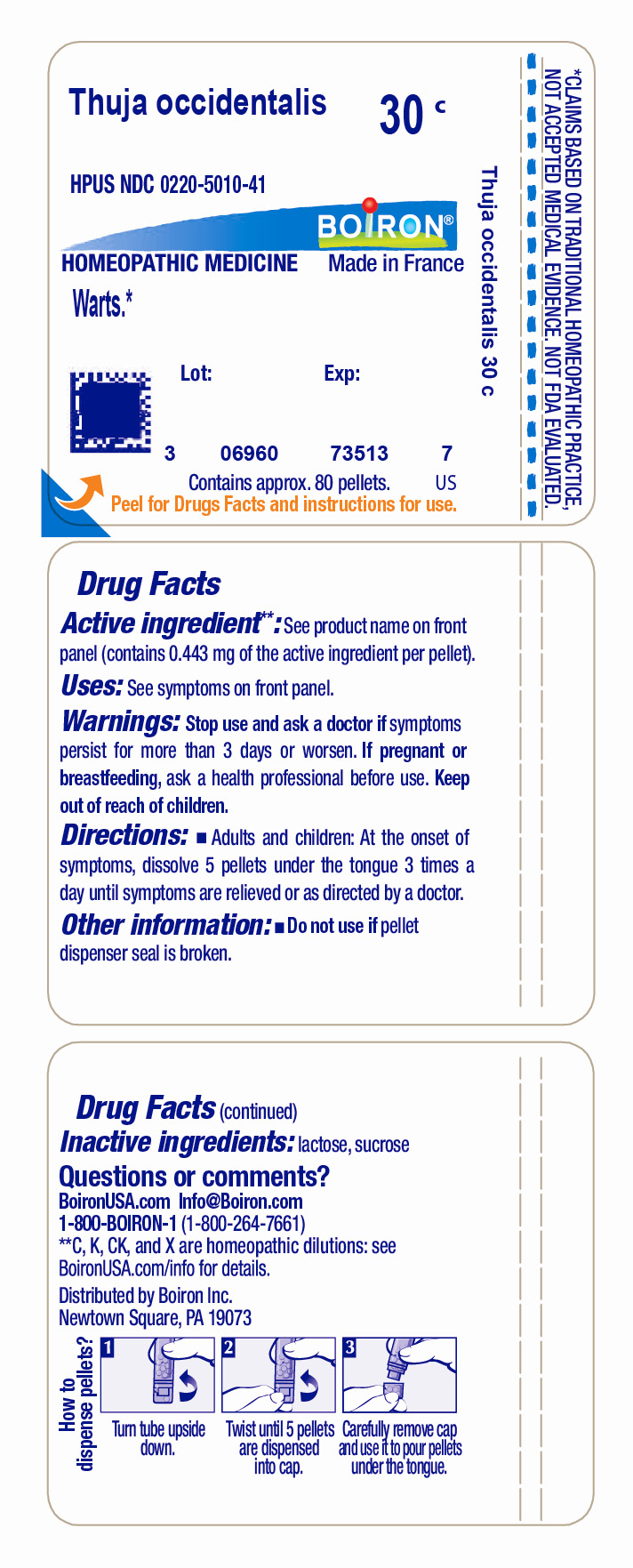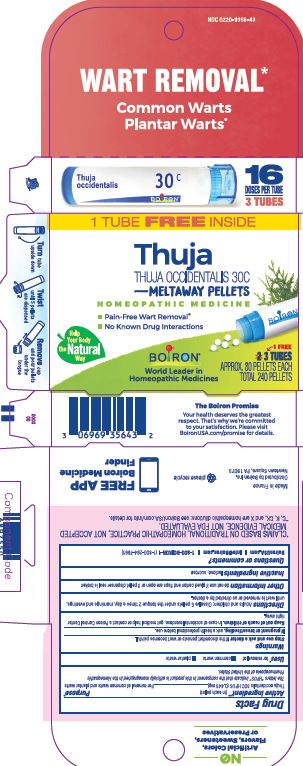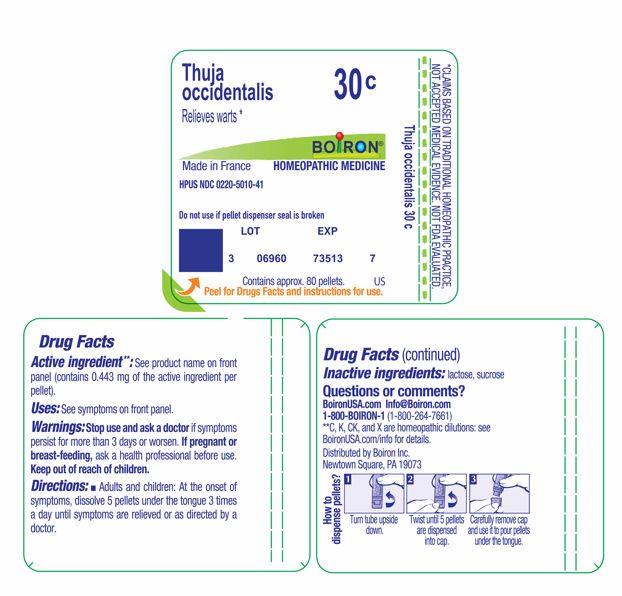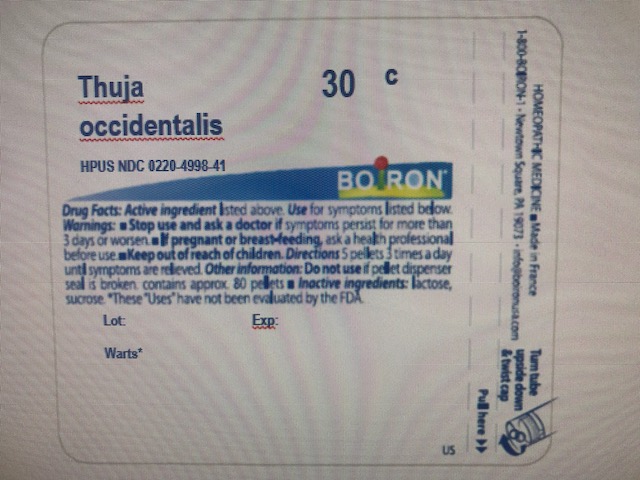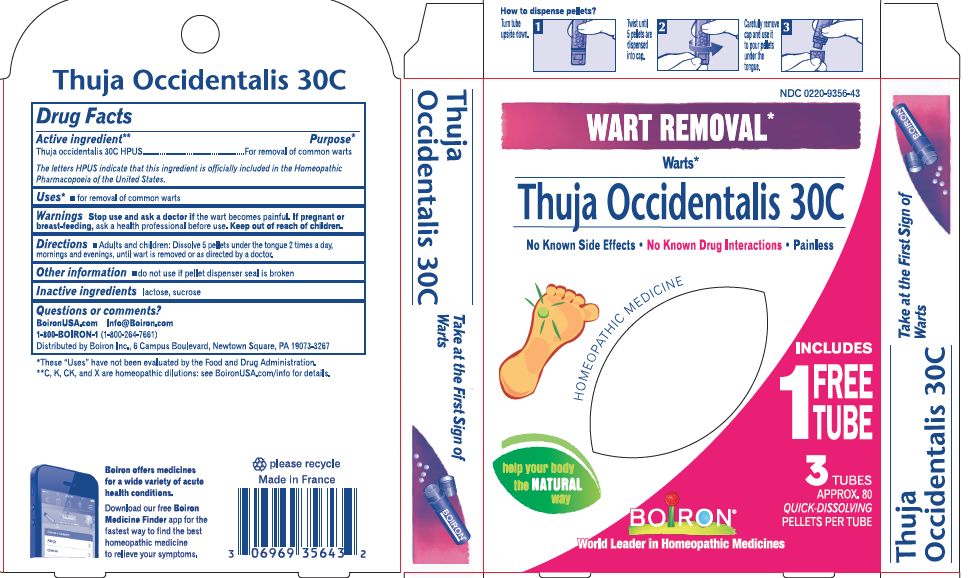 DRUG LABEL: Thuja occidentalis 30C
NDC: 0220-9356 | Form: PELLET
Manufacturer: Boiron
Category: homeopathic | Type: HUMAN OTC DRUG LABEL
Date: 20251121

ACTIVE INGREDIENTS: THUJA OCCIDENTALIS LEAFY TWIG 30 [hp_C]/30 [hp_C]
INACTIVE INGREDIENTS: LACTOSE; SUCROSE

Thuja occidentalis 30C BONUS PACK

Active ingredient** (in each pellet)

Thuja Occidentalis 30C HPUS (0.443)

The letters "HPUS" indicate that the component in this product are officially monographed in the Homeopathic Pharmacopoeia of the United States.

PURPOSE

Thuja Occidentalis 30C HPUS (0.443) ... For removal of common warts and plantar warts*

Uses*

for removal of

- common warts
- plantar warts

Stop use and ask a doctor if the discomfort persists or wart becomes painful.

Stop use and ask a doctor if symptoms persist for more than 3 days or worsen.

PREGNANCY OR BREAST FEEDING

If pregnant or breast-feeding, ask a health professional before use.

Keep out of reach of children. In case of accidental overdose, get medical help or contact a Poison Control Center right away.

DOSAGE AND ADMINISTRATION

Adults and children: Dissolve 5 pellets under the tongue 2 times a day, mornings and evenings, until wart is removed or as directed by a doctor.

Adults and children: At the onset of symptoms, dissolve 5 pellets under the tongue 3 times a day until symptoms are relieved or as directed by a doctor.

Do not use if glued carton end flaps are open or if pellet dispenser seal is broken.

Do not use if pellet dispenser seal is broken.

INACTIVE INGREDIENT

lactose, sucrose

QUESTIONS

Boironusa.com

info@boiron.com

1-800-BOIRON-1

1-800-264-7661

Distributed by Boiron Inc.

Newtown Square, PA 19073

*CLAIMS BASED ON TRADITIONAL HOMEOPATHIC PRACTICE NOT ACCEPTED MEDICAL EVIDENCE. NOT FDA EVALUATED.
**C,K,CK, and X are homeopathic dilutions: see BoironUSA.com/info for details.

Turn tube upside down, twist until 5 pellets are dispensed, Remove cap and pour pellets under the tongue

3 Tubes, Approx. 80 Pellets Each, Total 240 Pellets, 16 Doses per tube

Pain-Free Wart Removal*

No Known Drug Interactions

Common Warts, Plantar Warts*

Wart Removal*